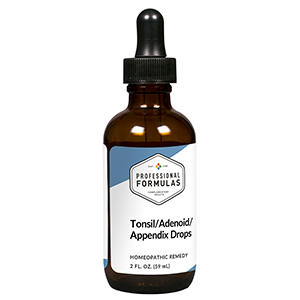 DRUG LABEL: Tonsil/Adenoid/Appendix Drops
NDC: 63083-5030 | Form: LIQUID
Manufacturer: Professional Complementary Health Formulas
Category: homeopathic | Type: HUMAN OTC DRUG LABEL
Date: 20190815

ACTIVE INGREDIENTS: BERBERIS AQUIFOLIUM ROOT BARK 3 [hp_X]/59 mL; ECHINACEA ANGUSTIFOLIA WHOLE 3 [hp_X]/59 mL; SUS SCROFA LYMPH 6 [hp_X]/59 mL; SUS SCROFA COLON 6 [hp_X]/59 mL; BOS TAURUS TONSIL 6 [hp_X]/59 mL
INACTIVE INGREDIENTS: ALCOHOL; WATER

HTAA

ACTIVE INGREDIENTS

Berberis aquifolium 3X
Echinacea angustifolia 3X
Adenoids 6X, 12X, 30X, 60X, 100X
Appendix 6X, 12X, 30X, 60X, 100X
Tonsils 6X, 12X, 30X, 60X, 100X

QUESTIONS

Professional Formulas

PO Box 2034 Lake Oswego, OR 97035

INDICATIONS

For the temporary relief of minor sore throat, cough, occasional headache, runny nose, mild abdominal pain, nausea or vomiting, loss of appetite, tiredness, or feelings of discomfort or uneasiness.*

PURPOSE

*Claims based on traditional homeopathic practice, not accepted medical evidence. Not FDA evaluated.

WARNINGS

Severe or persistent symptoms accompanied by a fever may be serious. Consult a doctor promptly. Keep out of the reach of children. In case of overdose, get medical help or contact a poison control center right away. If pregnant or breastfeeding, ask a healthcare professional before use.

Keep out of the reach of children.

PREGNANCY OR BREAST FEEDING

If pregnant or breastfeeding, ask a healthcare professional before use.

DIRECTIONS

Place drops under tongue 30 minutes before/after meals. Adults and children 12 years and over: Take 10 drops up to 3 times per day. Consult a physician for use in children under 12 years of age.

OTHER INFORMATION

Tamper resistant. If seal is broken, do not use. After opening, close container tightly and store at room temperature away from heat.

INACTIVE INGREDIENTS

20% ethanol, purified water.

LABEL

Est 1985

Professional Formulas

Complementary Health

Tonsil/Adenoid/Appendix Drops

Homeopathic Remedy

2 FL. OZ. (59 mL)